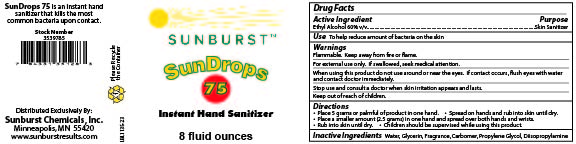 DRUG LABEL: SunDrops 75
NDC: 63621-356 | Form: GEL
Manufacturer: Sunburst Chemicals, Inc.
Category: otc | Type: HUMAN OTC DRUG LABEL
Date: 20251111

ACTIVE INGREDIENTS: ALCOHOL 0.6 mL/1 mL
INACTIVE INGREDIENTS: GLYCERIN; DIISOPROPYLAMINE; WATER; CARBOMER INTERPOLYMER TYPE A (ALLYL SUCROSE CROSSLINKED); PROPYLENE GLYCOL

SunDrops 75

Active Ingredient

Ethyl Alcohol 60% v/v

Purpose

Skin Sanitizer

Use

To help reduce amount of bacteria on the skin

Warnings

Flammable. Keep away from fire or flame.

For external use only. If swallowed, seek medical attention.

When using this product do not use around or near the eyes. If contact occurs, flush eyes with water and contact doctor immediately.

Stop use and consult a doctor when skin irritation appears and lasts.

Keep out of reach of children.

Directions

- Place 5 grams or palmful of product in one hand.
- Spread on hands and run into skin until dry.
- Place a smaller amount (2.5 grams) in one hand and spread over both hands and wrists.
- Rub into skin until dry.
- Children should be supervised while using this product.

Inactive Ingredients

Water, Glycerin, Fragrance, Carbomer, Propylene Glycol, Diisopropylamine